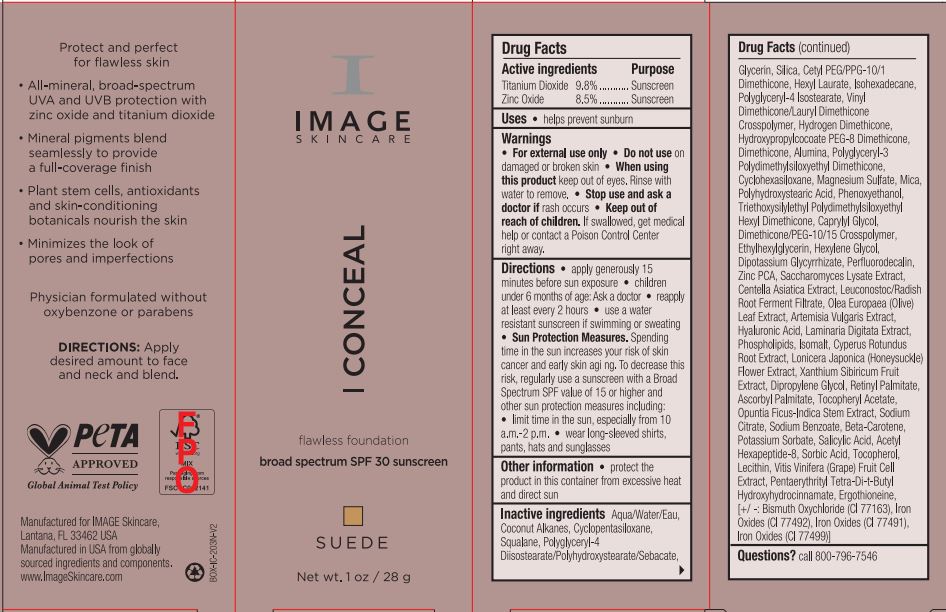 DRUG LABEL: I Conceal Flawless Foundation BS SPF 30 Sunscreen SUEDE
NDC: 62742-4244 | Form: CREAM
Manufacturer: Allure Labs
Category: otc | Type: HUMAN OTC DRUG LABEL
Date: 20240110

ACTIVE INGREDIENTS: ZINC OXIDE 8.5 g/100 g; TITANIUM DIOXIDE 9.8 g/100 g
INACTIVE INGREDIENTS: ARTEMISIA VULGARIS WHOLE; HYALURONIC ACID; LAMINARIA DIGITATA; VITAMIN A PALMITATE; .ALPHA.-TOCOPHEROL ACETATE; COCONUT ALKANES; CENTELLA ASIATICA TRITERPENOIDS; OLEA EUROPAEA LEAF; EGG PHOSPHOLIPIDS; ISOMALT; OPUNTIA FICUS-INDICA STEM; BETA CAROTENE; WATER; CYCLOMETHICONE 5; SQUALANE; POLYGLYCERYL-4 DIISOSTEARATE/POLYHYDROXYSTEARATE/SEBACATE; GLYCERIN; CETYL PEG/PPG-10/1 DIMETHICONE (HLB 4); HEXYLENE GLYCOL; HEXYL LAURATE; ISOHEXADECANE; POLYGLYCERYL-4 ISOSTEARATE; VINYL DIMETHICONE/METHICONE SILSESQUIOXANE CROSSPOLYMER; ALUMINUM OXIDE; POLYGLYCERYL-3 POLYDIMETHYLSILOXYETHYL DIMETHICONE (4000 MPA.S); CYCLOMETHICONE 6; MAGNESIUM SULFATE, UNSPECIFIED; MICA; PHENOXYETHANOL; TRIETHOXYSILYLETHYL POLYDIMETHYLSILOXYETHYL HEXYL DIMETHICONE; CAPRYLYL GLYCOL; DIMETHICONE/PEG-10/15 CROSSPOLYMER; ETHYLHEXYLGLYCERIN; GLYCYRRHIZINATE DIPOTASSIUM; PERFLUNAFENE; ZINC PIDOLATE; SACCHAROMYCES LYSATE; XANTHIUM SIBIRICUM FRUIT; SODIUM CITRATE; SODIUM BENZOATE; SALICYLIC ACID; LECITHIN, SOYBEAN; SORBIC ACID; TOCOPHEROL; WINE GRAPE; ACETYL HEXAPEPTIDE-8; BISMUTH OXYCHLORIDE; HYDROGEN DIMETHICONE (13 CST); HYDROXYPROPYLCOCOATE PEG-8 DIMETHICONE; DIMETHICONE; DIPROPYLENE GLYCOL; CYPERUS ROTUNDUS ROOT; LONICERA JAPONICA FLOWER; SILICON DIOXIDE; ERGOTHIONEINE; FERRIC OXIDE YELLOW; POTASSIUM SORBATE; PENTAERYTHRITOL TETRAKIS(3-(3,5-DI-TERT-BUTYL-4-HYDROXYPHENYL)PROPIONATE); FERRIC OXIDE RED; FERROSOFERRIC OXIDE; POLYHYDROXYSTEARIC ACID (2300 MW); LEUCONOSTOC/RADISH ROOT FERMENT FILTRATE

Drug Facts

Active Ingredient:

Titanium Dioxide – 9.8 %

Zinc Oxide - 8.5 %

Purpose: Sunscreen

INDICATIONS AND USAGE

Uses • helps prevent sunburn

Warnings • For external use only

Do not use on damaged or broken skin

When using this product keep out of eyes. Rinse with water to remove

Stop use and ask a doctor if rash occurs

Keep out of reach of children. If swallowed, get medical help or contact a Poison Control Center right away.

DOSAGE AND ADMINISTRATION

Directions • apply generously 15 minutes before sun exposure • children under 6 months of age: Ask a doctor • reapply at least every 2 hours • use a water resistant sunscreen if swimming or sweating

• Sun Protection Measures. Spending time in the sun increases your risk of skin cancer and early skin aging. To decrease this risk, regularly use a sunscreen with a Broad Spectrum SPF value of 15 or higher and other sun protection measures including: • limit time in the sun, especially from 10 a.m.-2 p.m. • wear long-sleeved shirts, pants, hats and sunglasses

Other information • protect the product in this container from excessive heat and direct sun

Inactive ingredients:

Water/Aqua/Eau, Cyclopentasiloxane, Coconut Alkanes, Squalane, Polyglyceryl-4 Diisostearate/Polyhydroxystearate/Sebacate, Glycerin, Silica, Cetyl PEG/PPG-10/1 Dimethicone, Hexyl Laurate, Isohexadecane, Polyglyceryl-4 Isostearate, Vinyl Dimethicone/Lauryl Dimethicone, Crosspolymer, Hydrogen Dimethicone, Hydroxypropylcocoate PEG-8 Dimethicone, Dimethicone, Alumina, Polyglyceryl-3 Polydimthylsiloxyethyl Dimethicone, Cyclohexasiloxane, Magnesium Sulfate, Mica, Polyhydroxysteraic Acid, Phenoxyethanol, Triethoxysilyethyl Polydimethylsiloxyethyl Hexyl Dimethicone, Caprylyl Glycol, Dimethicone/PEG-10/15 Crosspolymer, Ethylhexylglycerin, Hexylene Glycol, Dipotassium Glycyrrhizate, Perflurorodecalin, Zinc PCA, Saccharomyces Lysate Extract, Centella Asiatica Extract, Leuconostoc/Radish Root Ferment Filtrate, Olea Europea (Olive) Leaf Extract, Artemisia Vulgaris Extract , Hyaluronic Acid, Laminaria Digitata Extract, Phospholipids, Isomalt, Cyperus Rotundus Root Extract, Lonicera Japonica (Honeysuckle) Flower Extract, Xanthium Sibiricum Fruit Extract, Dipropylene Glycol, Retinyl Palmitate, Tococpheryl Acetate, Opuntia Ficus-Indica Stem Extract, Sodium Citrate, Sodium Benzoate, Beta-Carotene, Potassium Sorbate, Salicylic Acid, Acetyl Hexapeptide-8, Sorbic Acid, Tocopherol, Lecithin, Vitis Vinifera (Grape) Fruit Cell Extract, Pentaerythrityl Tetra-Di-T-Butyl Hydroxyhydrocinnamate, Ergothioneine, [+/ -: Bismuth Oxychloride (Ci 77163),Iron Oxide (Ci 77492), Iron Oxide (Ci 77491), Iron Oxide (Ci77499)]